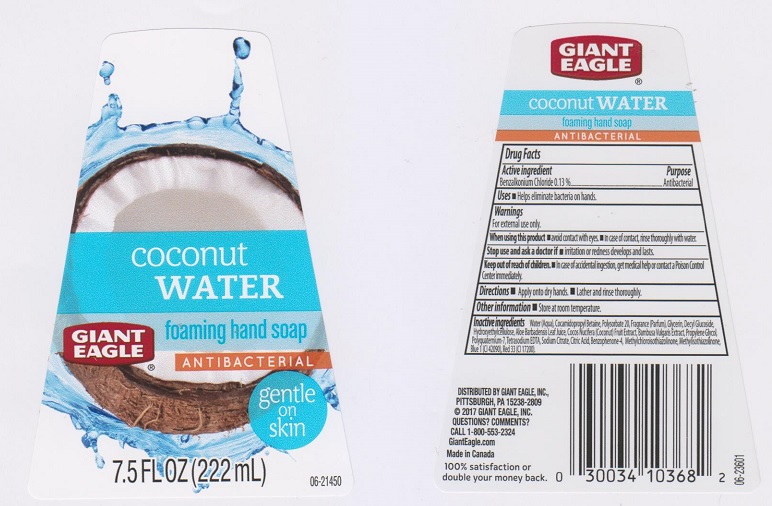 DRUG LABEL: Giant Eagle Coconut Water Foaming
NDC: 63148-842 | Form: LIQUID
Manufacturer: Apollo Health and Beauty Care Inc.
Category: otc | Type: HUMAN OTC DRUG LABEL
Date: 20170524

ACTIVE INGREDIENTS: BENZALKONIUM CHLORIDE 1.3 mg/1 mL
INACTIVE INGREDIENTS: WATER; COCAMIDOPROPYL BETAINE; POLYSORBATE 20; GLYCERIN; DECYL GLUCOSIDE; POWDERED CELLULOSE; ALOE VERA LEAF; COCONUT; BAMBUSA VULGARIS TOP; PROPYLENE GLYCOL; EDETATE SODIUM; SODIUM CITRATE; CITRIC ACID MONOHYDRATE; SULISOBENZONE; METHYLCHLOROISOTHIAZOLINONE; METHYLISOTHIAZOLINONE; FD&C BLUE NO. 1; D&C RED NO. 33

Drug Facts

Active ingredient

Benzalkonium Chloride 0.13%

Purpose

Antibacterial

Uses

- helps eliminate bacteria on hands.

Warnings

For external use only.

When using this product

- avoid contact with eyes
- in case of contact, rinse thoroughly with water

Stop use and ask a doctor if

- irritation or redness develops and lasts

Keep out of reach of children.

In case of accidental ingestion, get medical help or contact a Poison Control Center immediately.

Directions

- apply onto dry hands
- lather and rinse thoroughly

Other information

- store at room temperature

Inactive ingredients

Water (Aqua), Cocamidopropyl Betaine, Polysorbate 20, Fragrance (Parfum), Glycerin, Decyl Glucoside, Hydroxyethylcellulose, Aloe Barbadensis Leaf Juice, Cocos Nucifera (Coconut) Fruit Extract, Bambusa Vulgaris Extract, Propylene Glycol, Polyquaternium-7, Tetrasodium EDTA, Sodium Citrate, Citric Acid, Benzophenone-4, Methylchloroisothiazolinone, Methylisothiazolinone, Blue 1 (CI 42090), Red 33 (CI 17200).